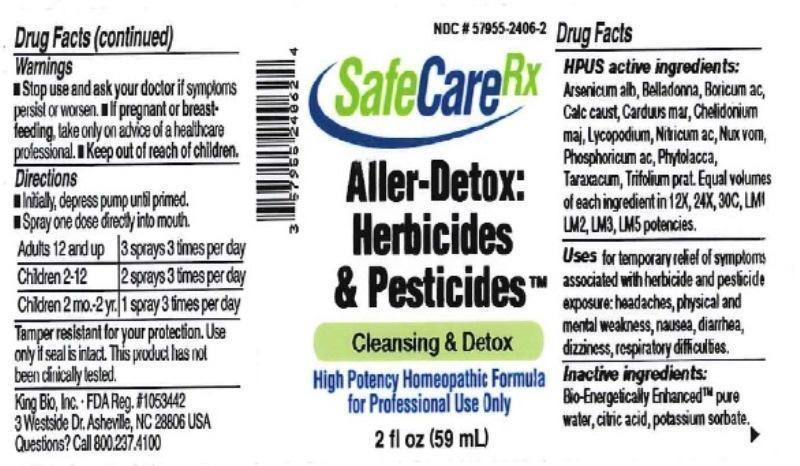 DRUG LABEL: Aller Detox Herbicides and Pesticides
NDC: 57955-2406 | Form: LIQUID
Manufacturer: King Bio Inc.
Category: homeopathic | Type: HUMAN OTC DRUG LABEL
Date: 20150616

ACTIVE INGREDIENTS: ARSENIC TRIOXIDE 12 [hp_X]/59 mL; ATROPA BELLADONNA 12 [hp_X]/59 mL; BORIC ACID 12 [hp_X]/59 mL; CALCIUM HYDROXIDE 12 [hp_X]/59 mL; MILK THISTLE 12 [hp_X]/59 mL; CHELIDONIUM MAJUS 12 [hp_X]/59 mL; LYCOPODIUM CLAVATUM SPORE 12 [hp_X]/59 mL; NITRIC ACID 12 [hp_X]/59 mL; STRYCHNOS NUX-VOMICA SEED 12 [hp_X]/59 mL; PHOSPHORIC ACID 12 [hp_X]/59 mL; PHYTOLACCA AMERICANA ROOT 12 [hp_X]/59 mL; TARAXACUM OFFICINALE 12 [hp_X]/59 mL; TRIFOLIUM PRATENSE FLOWER 12 [hp_X]/59 mL
INACTIVE INGREDIENTS: WATER; ANHYDROUS CITRIC ACID; POTASSIUM SORBATE

Aller Detox Herbicides and Pesticides™

ACTIVE INGREDIENT

Drug Facts__________________________________________________________________________________________________________

HPUS active ingredients: Arsenicum album, Belladonna, Boricum acidum, Calcarea caustica, Carduus marianus, Chelidonium majus, Lycopodium clavatum, Nitricum acidum, Nux vomica, Phosphoricum acidum, Phytolacca decandra, Taraxacum officinale, Trifolium pratense. Equal volumes of each ingredient in 12X, 24X, 30C, LM1, LM2, LM3, LM5 potencies.

INDICATIONS AND USAGE

Uses for temporary relief of symptoms associated with herbicide and pesticide exposure: headaches, physical and mental weakness, nausea, diarrhea, dizziness, respiratory difficulties.

Inactive Ingredients:

Bio-Energetically Enhanced™ pure water, citric acid and potassium sorbate.

Warnings

- Stop use and ask your doctor if symptoms persist or worsen.
- If pregnant or breast-feeding, take only on advice of a healthcare professional.

- Keep out of reach of children.

Directions

- Initially, depress pump until primed.
- Spray one dose directly into mouth.
- Adults 12 and up: 3 sprays 3 times per day
- Children 2-12: 2 sprays 3 times per day.
- Children 2 mo-2yr: 1 spray 3 times per day.

OTHER SAFETY INFORMATION

Tamper resistant for your protection. Use only if safety seal is intact. This product has not been clinically tested.

PURPOSE

Uses for temporary relief of symptoms associated with herbicide and pesticide exposure:

- headaches
- physical and mental weakness
- nausea
- diarrhea
- dizziness
- respiratory difficulties